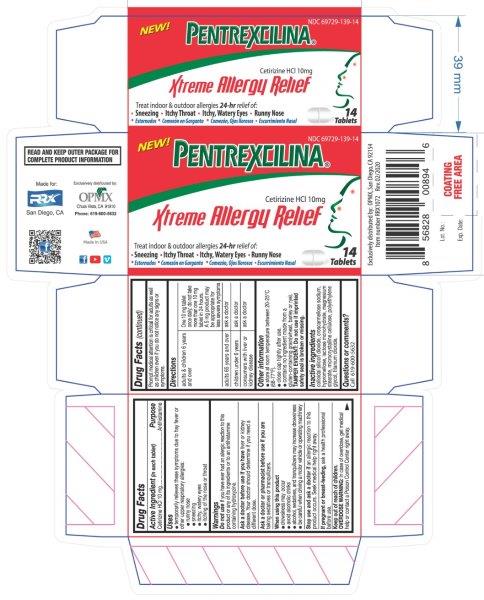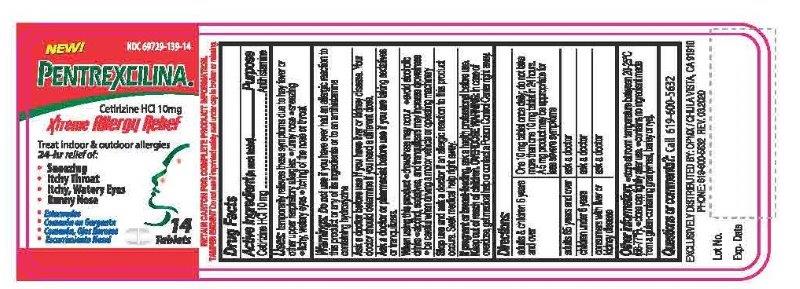 DRUG LABEL: Cetirizine hydrochloride
NDC: 69729-139 | Form: TABLET
Manufacturer: OPMX LLC
Category: otc | Type: HUMAN OTC DRUG LABEL
Date: 20240517

ACTIVE INGREDIENTS: CETIRIZINE HYDROCHLORIDE 10 mg/1 1
INACTIVE INGREDIENTS: POLYETHYLENE GLYCOL, UNSPECIFIED; LACTOSE MONOHYDRATE; CROSCARMELLOSE SODIUM; HYPROMELLOSE, UNSPECIFIED; CELLULOSE, MICROCRYSTALLINE; MAGNESIUM STEARATE; SILICON DIOXIDE; TITANIUM DIOXIDE

Pentrexcilina
Cetirizine HCl 10mg

ACTIVE INGREDIENT

Cetirizine HCl 10 mg

INACTIVE INGREDIENT

colloidal silicon dioxide, croscarmellose sodium, Hypromellose, lactose monohydrate, magnesium stearate, microcrystalline cellulose, polyethylene glycol, titanium dioxide

DOSAGE AND ADMINISTRATION

- adults & children 6 years and over: One 10 mg tablet once daily; do not take more than one 10 mg tablet in 24 hours. A 5 mg product may be appropriate for less severe symptoms
- adults 65 years and over: Ask a doctor
- children under 6 years: Ask a doctor
- consumers with liver or kidney disease: Ask a doctor

Do not use if you have ever had an allergic reaction to this product or any of its ingredients or to an antihistamine containing hydroxyzine.

Ask a doctor before use if you have liver or kidney disease. Your doctor should determine if you need a different dose.

Ask a doctor or pharmacist before use if you are taking sedatives or tranquilizers.

When using this product

■ drowsiness may occur

■ avoid alcoholic drinks

■ alcohol, sedatives, and tranquilizers may increase drowsiness

■ be careful when driving a motor vehicle or operating machinery

Stop use and ask a doctor if an allergic reaction to this product occurs. Seek medical help right away.

If pregnant or breast-feeding, ask a health professional before use.

Keep out of reach of children.

Keep out of reach of children.

OVERDOSE WARNING: In case of overdose, get medical help or contact a Poison Control Center right away. Prompt medical attention is critical for adults as well as children even if you do not notice any signs or symptoms.

PURPOSE

Antihistamine

OTHER SAFETY INFORMATION

■ store at room temperature between 20-25°C (68-77°F).

■ close cap tightly after use.

■ contains no ingredient made from a gluten-containing grain (wheat, barley or rye).

TAMPER EVIDENT: Do not use if imprinted safety seal is broken or missing.